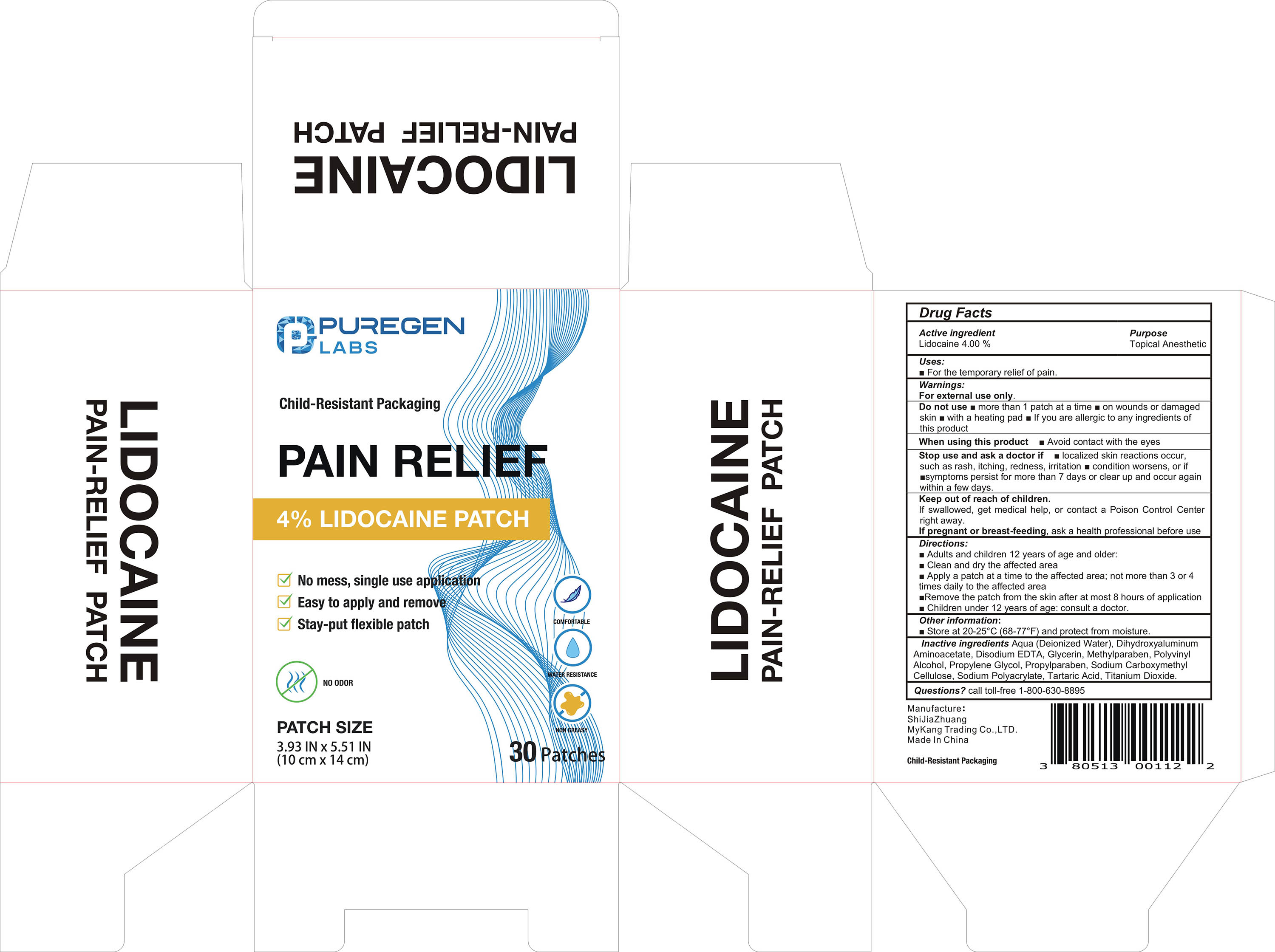 DRUG LABEL: Lidocaine Pain Relief Patch
NDC: 84664-001 | Form: PATCH
Manufacturer: ShiJiaZhuang MyKang Trading Co., LTD.
Category: otc | Type: HUMAN OTC DRUG LABEL
Date: 20240822

ACTIVE INGREDIENTS: LIDOCAINE 4 g/100 1
INACTIVE INGREDIENTS: EDETATE DISODIUM; POLYVINYL ALCOHOL, UNSPECIFIED; DIHYDROXYALUMINUM AMINOACETATE; CARBOXYMETHYLCELLULOSE SODIUM, UNSPECIFIED; GLYCERIN; SODIUM POLYACRYLATE (2500000 MW); METHYLPARABEN; PROPYLENE GLYCOL; TARTARIC ACID; PROPYLPARABEN; TITANIUM DIOXIDE; WATER

Lidocaine Pain Relief Patch

Lidocaine Pain Relief Patch

ACTIVE INGREDIENT

Lidocaine 4%

PURPOSE

Topical Anesthetic

INDICATIONS AND USAGE

For the temporary relief of pain.

WARNINGS

For external use only.

Do not use more than 1 patch at a time on wounds or damagedskin with a heating pad lf you are allergic to any ingredients ofthis product

WHEN USING

Avoid contact with the eyes When using this product

Stop use and ask a doctor if localized skin reactions occur,such as rash, itching, redness, irritation condition worsens, or if symptoms persist for more than 7 days or clear up and occur againwithin a few days.

KEEP OUT OF REACH OF CHILDREN

If swallowed, get medical help, or contact a Poison Control Centerright away.
If pregnant or breast-feeding, ask a health professional before use

DOSAGE AND ADMINISTRATION

Adults and children 12 years of age and older:
Clean and dry the affected area
Apply a patch at a time to the affected area; not more than 3 or 4times daily to the affected area
Remove the patch from the skin after at most 8 hours of application
Children under 12 years of age: consult a doctor.

STORAGE AND HANDLING

Store at 20-25°C(68-77°F)and protect from moisture.

INACTIVE INGREDIENT

dihydroxyaluminium aminoacetate
disodium EDTA
Methylparaben
polyvinyl alcohol
propylene glycol
sodium carboxymethyl cellulose
sodium polyacrylate
propyl paraben
titanium dioxide
tartaric acid
Glycerin
purified water